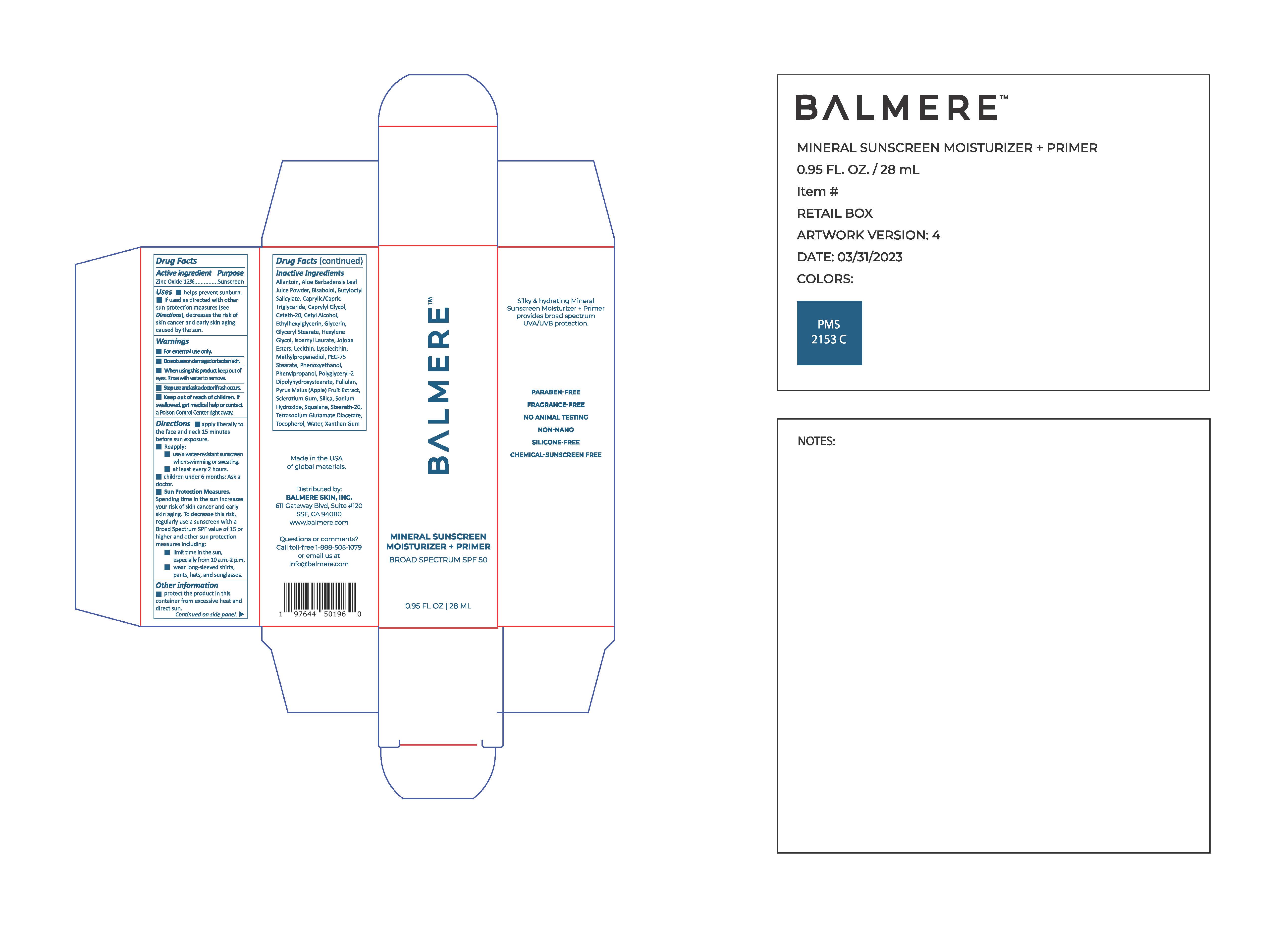 DRUG LABEL: Balmere Mineral Sunscreen Moisturizer Primer
NDC: 83241-1039 | Form: LOTION
Manufacturer: Balmere
Category: otc | Type: HUMAN OTC DRUG LABEL
Date: 20251113

ACTIVE INGREDIENTS: ZINC OXIDE 132 mg/1 mL
INACTIVE INGREDIENTS: LECITHIN, SOYBEAN; POLYGLYCERYL-2 DIPOLYHYDROXYSTEARATE; HYDROLYZED JOJOBA ESTERS (ACID FORM); METHYLPROPANEDIOL; CAPRYLYL GLYCOL; PHENYLPROPANOL; XANTHAN GUM; ISOAMYL LAURATE; HEXYLENE GLYCOL; TOCOPHEROL; CETYL ALCOHOL; ETHYLHEXYLGLYCERIN; GLYCERIN; SILICON DIOXIDE; WATER; .ALPHA.-BISABOLOL, (+)-; BUTYLOCTYL SALICYLATE; CETETH-20; PULLULAN; SQUALANE; STEARETH-20; CYCLODEXTRINS

Balmere Mineral Sunscreen Moisturizer + Primer